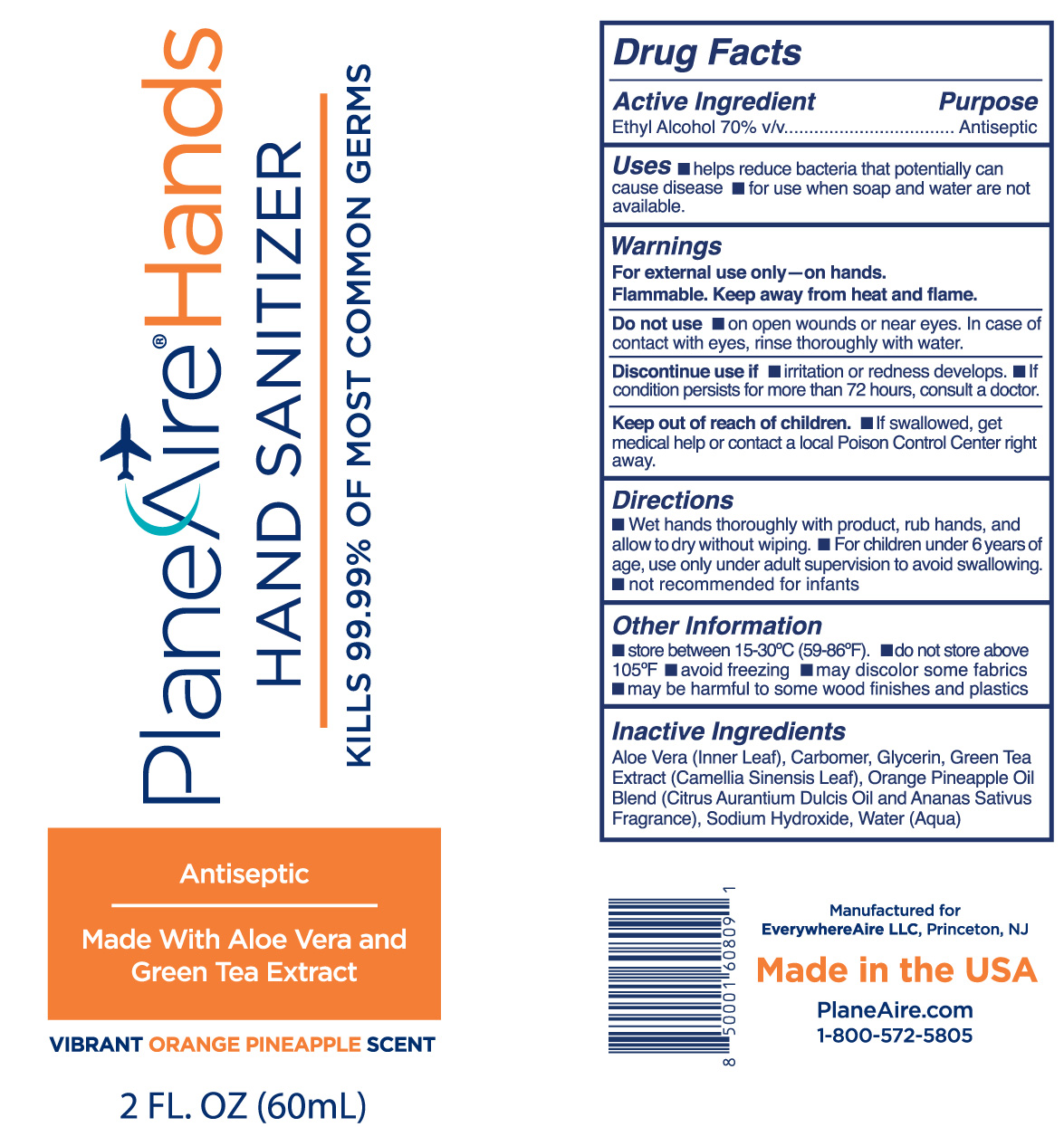 DRUG LABEL: Hand Sanitizer
NDC: 80335-103 | Form: GEL
Manufacturer: EverywhereAire LLC
Category: otc | Type: HUMAN OTC DRUG LABEL
Date: 20231220

ACTIVE INGREDIENTS: ALCOHOL 70 mL/100 mL
INACTIVE INGREDIENTS: GLYCERIN; WATER; ALOE VERA LEAF POLYSACCHARIDES; GREEN TEA LEAF; ORANGE OIL; CARBOMER 980; SODIUM HYDROXIDE; PINEAPPLE

PlaneAire Hands gel Orange Pineapp aloe green tea

This is a hand sanitizer

Active Ingredient(s)

Alcohol 70% v/v

Purpose

Antiseptic

Use

helps reduce bacteria that potentially can cause disease. For use when soap and water are not available.

Do not use

- in children less than 2 months of age
- on open skin wounds

Warnings

For external use only.- on hands. Flammable. Keep away from heat and flame

Do not use on open wounds or near eyes. In case of contact with eyes, rinse eyes thoroughly with water.
Discontinue use if irritation or rash develops. If condtion persits for more than 72 hours, consult a doctor.
Keep out of reach of children. If swallowed, get medical help or contact a local Poison Control Center right away.

Stop use and ask a doctor if irritation or rash occurs. These may be signs of a serious condition.

Keep out of reach of children. If swallowed, get medical help or contact a Poison Control Center right away.

Directions

- Wet hands thoroughly with product, rub hands, and allow to dry without wiping.
- For children under 6 years of age, use only under adult supervision to avoid swallowing.
- not recommended for infants

Other information

- Store between 15-30C (59-86F)
- Do not store above 105F
- avoid freezing
- may discolor some fabrics
- may be harmful to some wood finishes and plastics

Inactive ingredients

Aloe vera inner leaf, Carbomer, Glycerin, Green tea extract, Orang eoil, Pineappleoil, Sodium hydroxide, Water